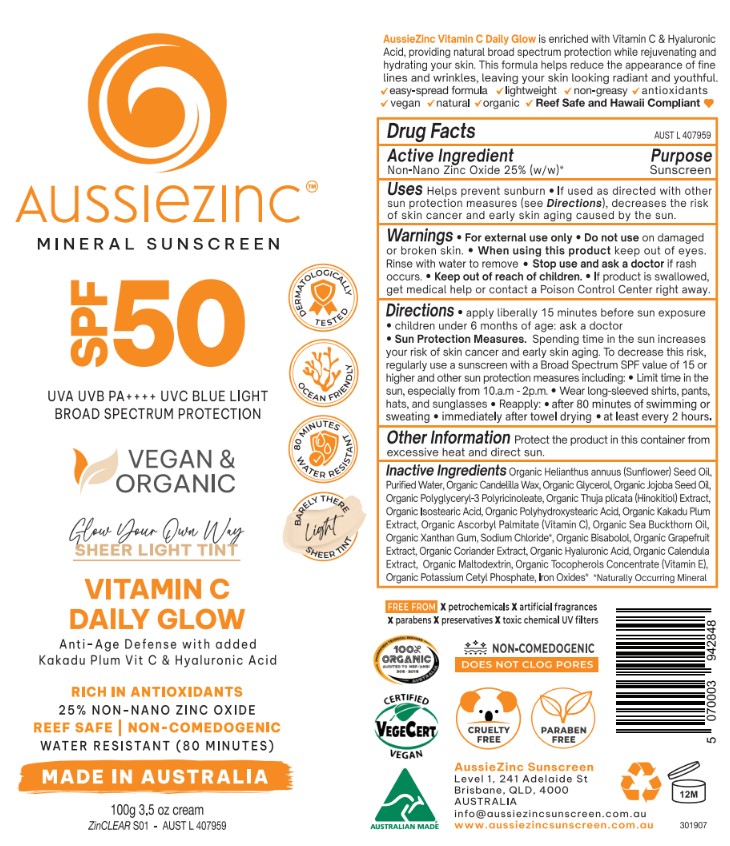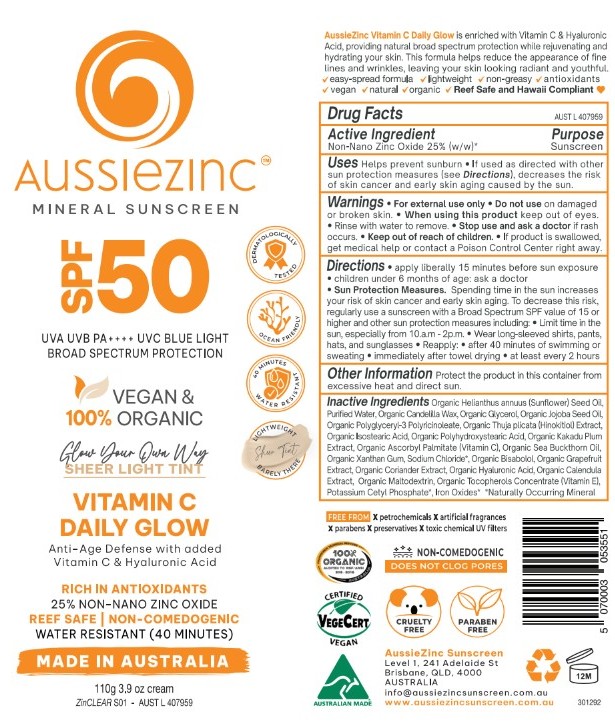 DRUG LABEL: AussieZinc Mineral Sunscreen Vegan and Organic Anti-Aging - Light Tint
NDC: 83252-097 | Form: CREAM
Manufacturer: VEGANIC SKN LIMITED
Category: otc | Type: HUMAN OTC DRUG LABEL
Date: 20251023

ACTIVE INGREDIENTS: ZINC OXIDE 25 kg/100 kg
INACTIVE INGREDIENTS: CITRUS PARADISI (GRAPEFRUIT) SEED OIL; HELIANTHUS ANNUUS (SUNFLOWER) SEED OIL; MALTODEXTRIN; JOJOBA OIL; HIPPOPHAE RHAMNOIDES SEED OIL; TOCOPHEROL; WATER; POLYHYDROXYSTEARIC ACID (2300 MW); ISOSTEARIC ACID; CANDELILLA WAX; SODIUM HYALURONATE; SODIUM CHLORIDE; GLYCERIN; POLYGLYCERYL-3 RICINOLEATE; POTASSIUM CETYL PHOSPHATE; CALENDULA OFFICINALIS FLOWERING TOP; SODIUM ASCORBATE; XANTHAN GUM; KAKADU PLUM; FERRIC OXIDE RED; BISABOLOL; SODIUM HINOKITIOL; FERRIC OXIDE YELLOW; FERROSOFERRIC OXIDE; CORIANDER OIL

AussieZinc Mineral Sunscreen Vegan and Organic Anti-Aging - Light Tint

ACTIVE INGREDIENT

Zinc oxide 25%

WARNINGS

For external use only.

Do not use on damaged r broken skin.

When using this product keep out of eyes. Rinse with water to remove.
Stop use and ask a doctor if rash occurs.

Keep out of reach of children.

If product is swallowed, get medical help or contact a Poison Control Center right away.

Keep out of reach of children.

INACTIVE INGREDIENT

See ingredients on label